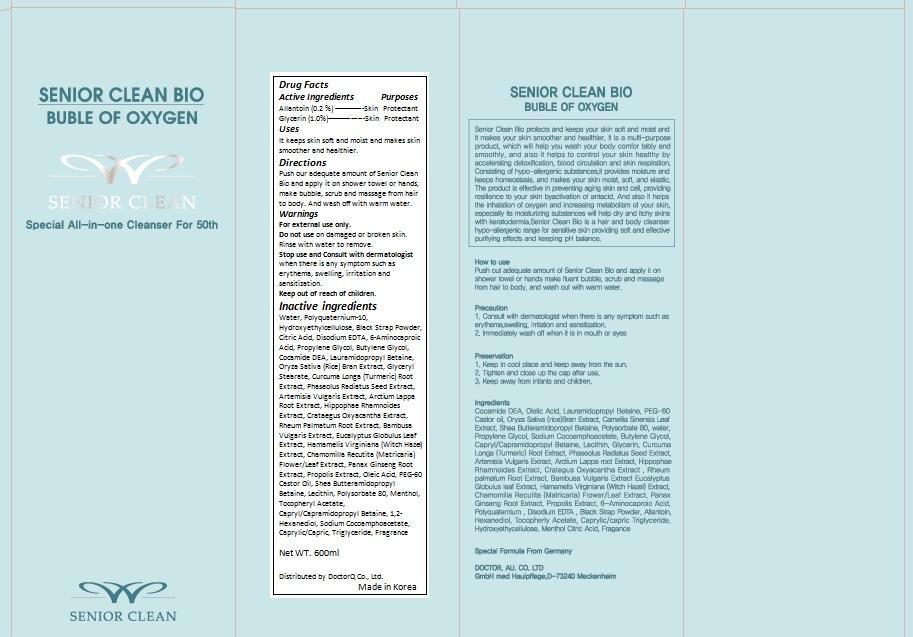 DRUG LABEL: Seniorclean Bio
NDC: 69405-001 | Form: GEL
Manufacturer: DoctorQ Co., Ltd.
Category: otc | Type: HUMAN OTC DRUG LABEL
Date: 20150202

ACTIVE INGREDIENTS: ALLANTOIN 0.12 mg/600 mL; GLYCERIN 6 mg/600 mL
INACTIVE INGREDIENTS: WATER; POLYQUATERNIUM-10 (1000 MPA.S AT 2%); HYDROXYETHYL CELLULOSE (100 MPA.S AT 2%); SPANISH SARDINE; CITRIC ACID MONOHYDRATE; EDETATE DISODIUM; BUTYLENE GLYCOL; AMINOCAPROIC ACID; PROPYLENE GLYCOL; COCO DIETHANOLAMIDE; Lauramidopropyl Betaine; RICE BRAN; GLYCERYL MONOSTEARATE; TURMERIC; MUNG BEAN; ARTEMISIA VULGARIS ROOT; ARCTIUM LAPPA ROOT; HIPPOPHAE RHAMNOIDES FRUIT; CRATAEGUS LAEVIGATA WHOLE; RHEUM PALMATUM ROOT; BAMBUSA VULGARIS TOP; EUCALYPTUS GLOBULUS LEAF; HAMAMELIS VIRGINIANA TOP; MATRICARIA RECUTITA FLOWERING TOP; ASIAN GINSENG; PROPOLIS WAX; TETRAHYDROFURFURYL OLEATE; PEG-60 CASTOR OIL; EGG PHOSPHOLIPIDS; POLYSORBATE 80; MENTHOL; 1,2-HEXANEDIOL; .ALPHA.-TOCOPHEROL ACETATE; CAPRYL/CAPRAMIDOPROPYL BETAINE; SODIUM COCOAMPHOACETATE; MEDIUM-CHAIN TRIGLYCERIDES

Drug Facts

ACTIVE INGREDIENT

Allantoin 0.2%

Glycerin 1%

PURPOSE

Skin Protectant

INDICATIONS AND USAGE

It keeps skin soft and moist and makes skin smoother and healthier.

WARNINGS

For external use only.

Do not use on damaged or broken skin.

Stop use and Consult with dermatologist when there is any symptom such as erythema, swelling, irritation and sensitization.

Keep out of reach of children.

When using this product, keep out of eyes.

INSTRUCTIONS FOR USE

Push our adequate amount of Senior Clean Bio and apply it on shower towel or hands, make bubble, scrub and massage from hair to body. And wash off with warm water.

INACTIVE INGREDIENT

Water, Polyquaternium-10, Hydroxyethylcellulose, Black Strap Powder, Citric Acid, Disodium EDTA, 6-Aminocaproic Acid, Propylene Glycol, Butylene Glycol, Cocamide DEA, Lauramidopropyl Betaine, Oryza Sativa (Rice) Bran Extract, Glyceryl Stearate, Curcuma Longa (Turmeric) Root Extract, Phaseolus Radiatus Seed Extract, Artemisia Vulgaris Extract, Arctium Lappa Root Extract, Hippophae Rhamnoides Extract, Crataegus Oxyacantha Extract, Rheum Palmatum Root Extract, Bambusa Vulgaris Extract, Eucalyptus Globulus Leaf Extract, Hamamelis Virginiana (Witch Hazel) Extract, Chamomilla Recutita (Matricaria) Flower/Leaf Extract, Panax Ginseng Root Extract, Propolis Extract, Oleic Acid, PEG-60 Castor Oil, Shea Butteramidopropyl Betaine, Lecithin, Polysorbate 80, Menthol, Tocopheryl Acetate, Capryl/Capramidopropyl Betaine, 1,2-Hexanediol, Sodium Cocoamphoacetate, Caprylic/Capric, Triglyceride, Fragrance

DOSAGE AND ADMINISTRATION

Apply appropriate amount when taking a shower.